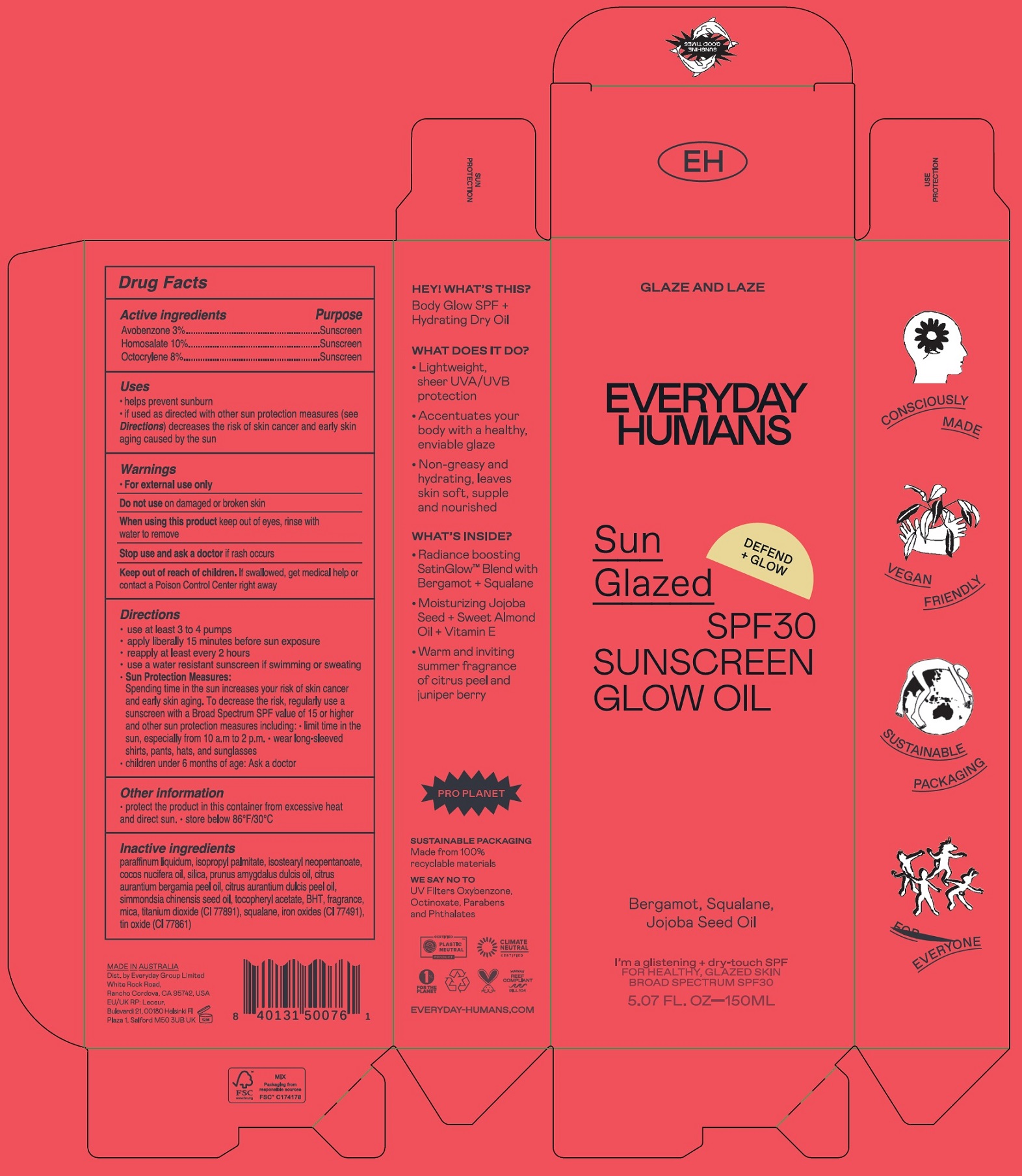 DRUG LABEL: Sun Glazed SPF 30 Sunscreen Glow Oil
NDC: 72098-007 | Form: OIL
Manufacturer: EVERYDAY GROUP LIMITED
Category: otc | Type: HUMAN OTC DRUG LABEL
Date: 20251204

ACTIVE INGREDIENTS: AVOBENZONE 30 mg/1 mL; HOMOSALATE 100 mg/1 mL; OCTOCRYLENE 80 mg/1 mL
INACTIVE INGREDIENTS: MINERAL OIL; ISOPROPYL PALMITATE; ISOSTEARYL NEOPENTANOATE; SILICON DIOXIDE; JOJOBA OIL; .ALPHA.-TOCOPHEROL ACETATE; BUTYLATED HYDROXYTOLUENE; MICA; TITANIUM DIOXIDE; SQUALANE; FERRIC OXIDE RED; STANNIC OXIDE

Sun Glazed SPF 30 Sunscreen Glow Oil

Active ingredients

Avobenzone 3% Homosalate 10% Octocrylene 8%

Purpose

Sunscreen

Uses

- helps prevent sunburn
- if used as directed with other sun protection measures (see) decreases the risk of skin cancer and early skin aging caused by the sun Directions

Warnings

- For external use only

Do not use

on damaged or broken skin

When using this product

keep out of eyes, rinse with water to remove

Stop use and ask a doctor

if rash occurs

Keep out of reach of children.

If swallowed, get medical help or contact a Poison Control Center right away

Directions

- use at least 3 to 4 pumps
- apply liberally 15 minutes before sun exposure
- reapply at least every 2 hours
- use a water resistant sunscreen if swimming or sweating
- Sun Protection Measures:
- Spending time in the sun increases your risk of skin cancer and early skin aging. To decrease the risk, regularly use a sunscreen with a Broad Spectrum SPF value of 15 or higher and other sun protection measures including:
- limit time in the sun, especially from 10 a.m. to 2 p.m.
- wear long-sleeved shirts, pants, hats, and sunglasses
- children under 6 months of age: Ask a doctor

Other information

- protect the product in this container from excessive heat and direct sun.
- store below 86°F/30° C

Inactive ingredients

paraffinum liquidum, isopropyl palmitate, isosterayl neopentanoate, cocos nucifera oil, silica, prunus amygdalus dulcis oil, citrus aurantium bergamia peel oil, citrus aurantium dulcis peel oil, simmondsia chinensis seed oil, tocopheryl acetate, BHT, fragrance, mica, titanium dioxide (CI 77891), squalane, iron oxides (CI 77491), tin oxide (CI 77861)